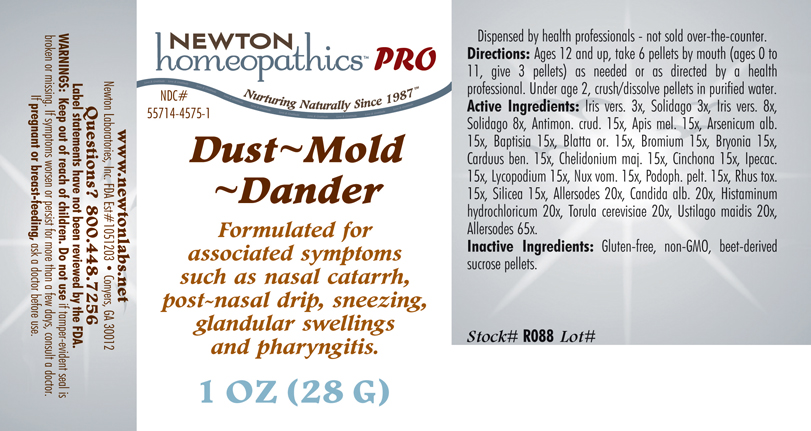 DRUG LABEL: Dust - Mold - Dander 
NDC: 55714-4575 | Form: PELLET
Manufacturer: Newton Laboratories, Inc.
Category: homeopathic | Type: HUMAN PRESCRIPTION DRUG LABEL
Date: 20110601

ACTIVE INGREDIENTS: Felis Catus Skin 65 [hp_X]/1 g; Canis Lupus Familiaris Skin 65 [hp_X]/1 g; Oryctolagus Cuniculus Skin 65 [hp_X]/1 g; Equus Caballus Skin 65 [hp_X]/1 g; Serinus Canaria Feather 65 [hp_X]/1 g; Gallus Gallus Feather 65 [hp_X]/1 g; Anas Platyrhynchos Feather 65 [hp_X]/1 g; Anser Anser Feather 65 [hp_X]/1 g; Melopsittacus Undulatus Feather 65 [hp_X]/1 g; Phasianus Colchicus Feather 65 [hp_X]/1 g; Meleagris Gallopavo Feather 65 [hp_X]/1 g; Felis Catus Hair 65 [hp_X]/1 g; Human Dander 65 [hp_X]/1 g; Canis Lupus Familiaris Hair 65 [hp_X]/1 g; Equus Caballus Hair 65 [hp_X]/1 g; Oryctolagus Cuniculus Hair 65 [hp_X]/1 g; Human Hair 65 [hp_X]/1 g; Human Skin 65 [hp_X]/1 g; Sheep Wool 65 [hp_X]/1 g; Bos Taurus Hair 65 [hp_X]/1 g; Capra Hircus Hair 65 [hp_X]/1 g; Cavia Porcellus Hair 65 [hp_X]/1 g; Mesocricetus Auratus Hair 65 [hp_X]/1 g; Wheat Gluten 20 [hp_X]/1 g; Aspergillus Niger Var. Niger 20 [hp_X]/1 g; Cladosporium Herbarum 20 [hp_X]/1 g; House Dust 20 [hp_X]/1 g; Candida Albicans 20 [hp_X]/1 g; Histamine Dihydrochloride 20 [hp_X]/1 g; Saccharomyces Cerevisiae 20 [hp_X]/1 g; Ustilago Maydis 20 [hp_X]/1 g; Antimony Trisulfide 15 [hp_X]/1 g; Apis Mellifera 15 [hp_X]/1 g; Arsenic Trioxide 15 [hp_X]/1 g; Baptisia Tinctoria Root 15 [hp_X]/1 g; Blatta Orientalis 15 [hp_X]/1 g; Bromine 15 [hp_X]/1 g; Bryonia Alba Root 15 [hp_X]/1 g; Centaurea Benedicta 15 [hp_X]/1 g; Chelidonium Majus 15 [hp_X]/1 g; Cinchona Officinalis Bark 15 [hp_X]/1 g; Ipecac 15 [hp_X]/1 g; Lycopodium Clavatum Spore 15 [hp_X]/1 g; Strychnos Nux-vomica Seed 15 [hp_X]/1 g; Podophyllum 15 [hp_X]/1 g; Toxicodendron Pubescens Leaf 15 [hp_X]/1 g; Silicon Dioxide 15 [hp_X]/1 g; Iris Versicolor Root 8 [hp_X]/1 g; Solidago Virgaurea Flowering Top 8 [hp_X]/1 g
INACTIVE INGREDIENTS: Sucrose

Dust - Mold - Dander

INDICATIONS & USAGE SECTION

Formulated for associated symptoms such as nasal catarrh, post-nasal drip, sneezing, glandular swellings and pharyngitis.

DOSAGE & ADMINISTRATION SECTION

Directions: Ages 12 and up, take 6 pellets by mouth (ages 0 to 11, give 3 pellets) as needed or as directed by a health professional. Under age 2, crush/dissolve pellets in purified water.

OTC - ACTIVE INGREDIENT SECTION

Allersodes 65x, Allersodes 20x, Candida alb. 20x, Histaminum hydrochloricum 20x, Torula cerevisiae 20x, Ustilago maidis 20x, Antimon. crud. 15x, Apis mel. 15x, Arsenicum alb. 15x, Baptisia 15x, Blatta or. 15x, Bromium 15x, Bryonia 15x, Carduus ben. 15x, Chelidonium maj. 15x, Cinchona 15x, Ipecac. 15x, Lycopodium 15x, Nux vom. 15x, Podoph. pelt. 15x, Rhus tox. 15x, Silicea 15x, Iris versicolor 8x, Solidago 8x, Iris versicolor 3x, Solidago 3x.

OTC - PURPOSE SECTION

Formulated for associated symptoms such as nasal catarrh, post-nasal drip, sneezing, glandular swellings and pharyngitis.

INACTIVE INGREDIENT SECTION

Gluten-free, non-GMO, beet-derived sucrose pellets.

QUESTIONS SECTION

www.newtonlabs.net Newton Laboratories, Inc. FDA Est # 1051203 - Conyers, GA 30012
Questions? 1.800.448.7256

WARNINGS SECTION

Warning: Keep our of reach of children. Do not use if tamper-evident seal is broken or missing. If symptoms worsen or persist for more than a few days, consult a doctor. If pregnant or breast-feeding, ask a doctor before use.

OTC - PREGNANCY OR BREAST FEEDING SECTION

If pregnant or breast-feeding, ask a doctor before use.

OTC - KEEP OUT OF REACH OF CHILDREN SECTION

Keep out of reach of children.